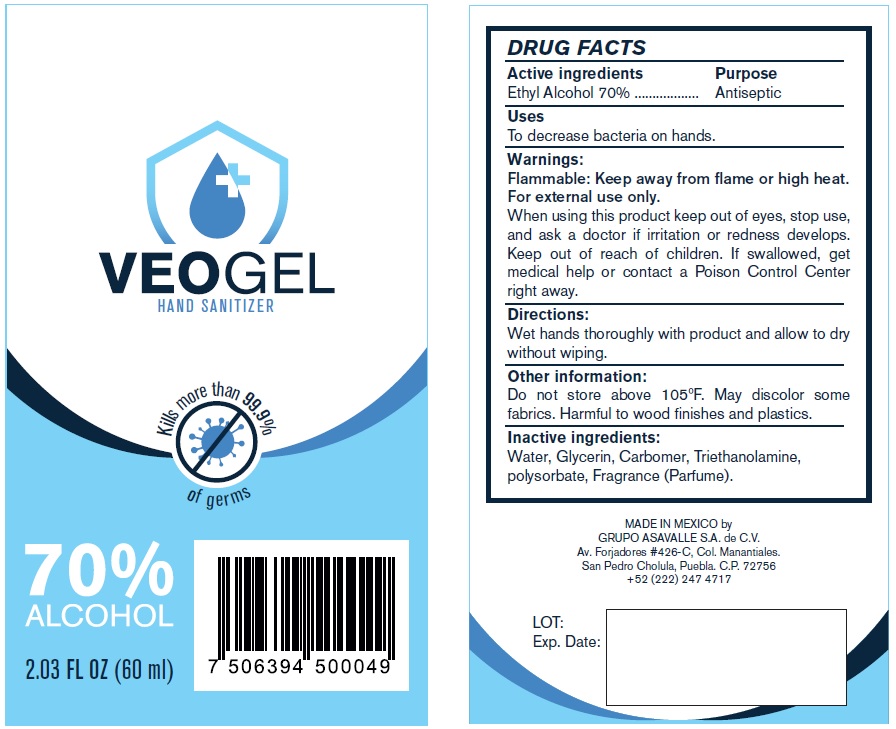 DRUG LABEL: Veogel Hand Sanitizer 70% Alcohol
NDC: 78244-002 | Form: GEL
Manufacturer: Grupo Asavalle, S.A. de C.V.
Category: otc | Type: HUMAN OTC DRUG LABEL
Date: 20200817

ACTIVE INGREDIENTS: ALCOHOL 0.7 mL/1 mL
INACTIVE INGREDIENTS: WATER; GLYCERIN; CARBOMER HOMOPOLYMER, UNSPECIFIED TYPE; TROLAMINE; POLYSORBATE 20

Veogel Hand Sanitizer 70% Alcohol

Active ingredients

Ethyl Alcohol 70%

Purpose

Antiseptic

Uses

To decrease bacteria on hands.

Warnings:

Flammable: Keep away from flame or high heat. For external use only.

When using this product

keep out of eyes, stop use, and ask a doctor if irritation or redness develops.

Keep out of reach of children.

If swallowed, get medical help or contact a Poison Control Center right away.

Directions:

Wet hands thoroughly with product and allow to dry without wiping.

Other information:

Do not store above 105ºF. May discolor some fabrics. Harmful to wood finishes and plastics.

Inactive ingredients:

Water, Glycerin, Carbomer, Triethanolamine, polysorbate, Fragrance (Parfume).